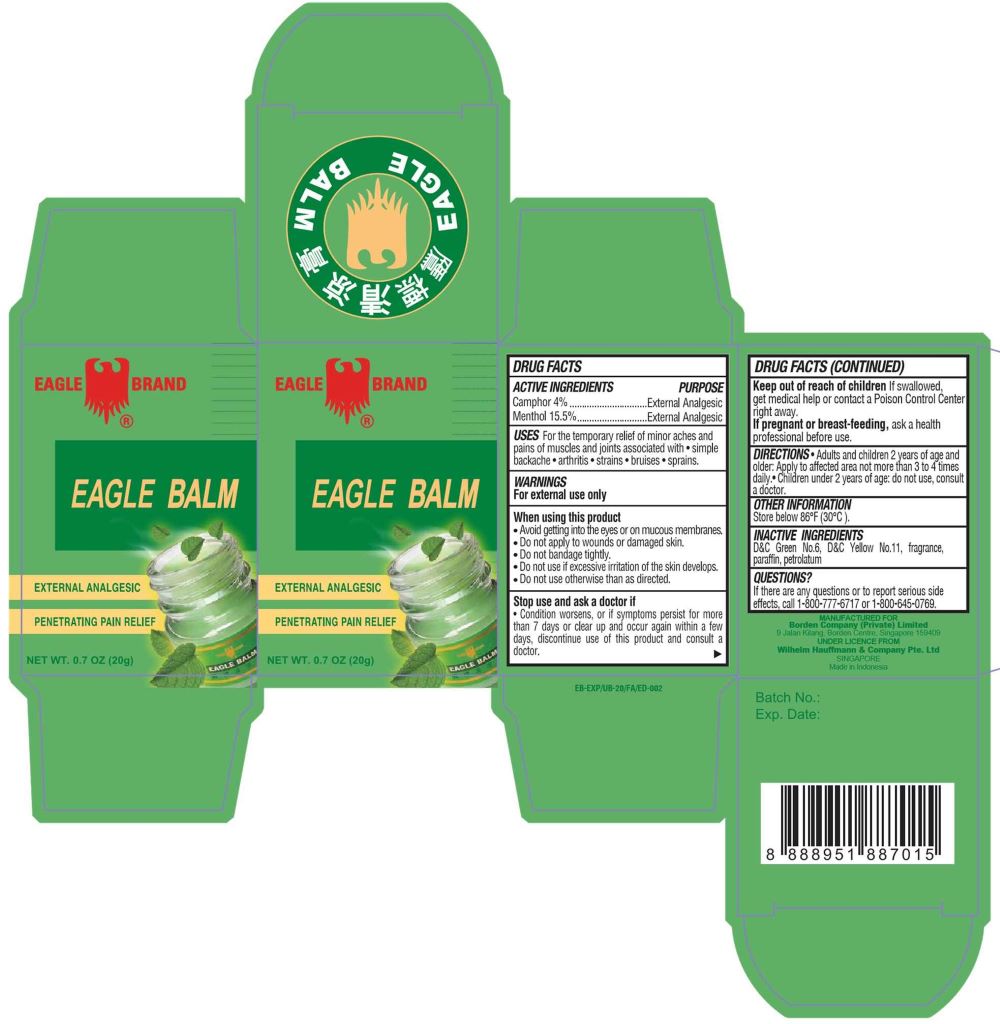 DRUG LABEL: Eagle Brand
NDC: 60954-201 | Form: OINTMENT
Manufacturer: PT. EAGLE INDO PHARMA
Category: otc | Type: HUMAN OTC DRUG LABEL
Date: 20250106

ACTIVE INGREDIENTS: CAMPHOR (SYNTHETIC) 4 g/100 g; MENTHOL 15.5 g/100 g
INACTIVE INGREDIENTS: D&C YELLOW NO. 11; PARAFFIN; PETROLATUM; D&C GREEN NO. 6; EUCALYPTUS OIL

Eagle Brand Eagle Balm

Active Ingredients

- Camphor 4%
- Menthol 15.5%

Purpose

External Analgesic

Uses

For the temporary relief of minor aches and pains of muscles and joints associated with • simple backache • arthritis • strains • bruises • sprains.

Warnings

For external use only

When using this product

- Avoid contact with eyes and mucous membranes.
- Do not apply to wounds or damaged skin.
- Do not bandage tightly.
- Do not use if excessive irritation of the skin develops.
- Do not use otherwise than as directed.

Stop use and ask doctor if

Condition worsens, or if symptoms persist for more than 7 days or clear up and occur again within a few days, discontinue use of this product and consult a doctor.

Keep out of reach of children

If swallowed, get medical help or contact a Poison Control Center right away.

If pregnant or breast-feeding

Ask a health professional before use.

Directions

• Adults and children 2 years of age and older: Apply to affected area not more than 3 to 4 times daily.

• Children under 2 years of age: do not use, consult a doctor.

Other information

Store below 86°F (30°C).

Inactive ingredients

D&C Green No.6, D&C Yellow No.11, fragrance, paraffin, petrolatum

Questions?

If there are any questions or to report serious side effects, call 1-800-777-6717 or 1-800-645-0769.

Package Label

20g NDC: 60954-201-20